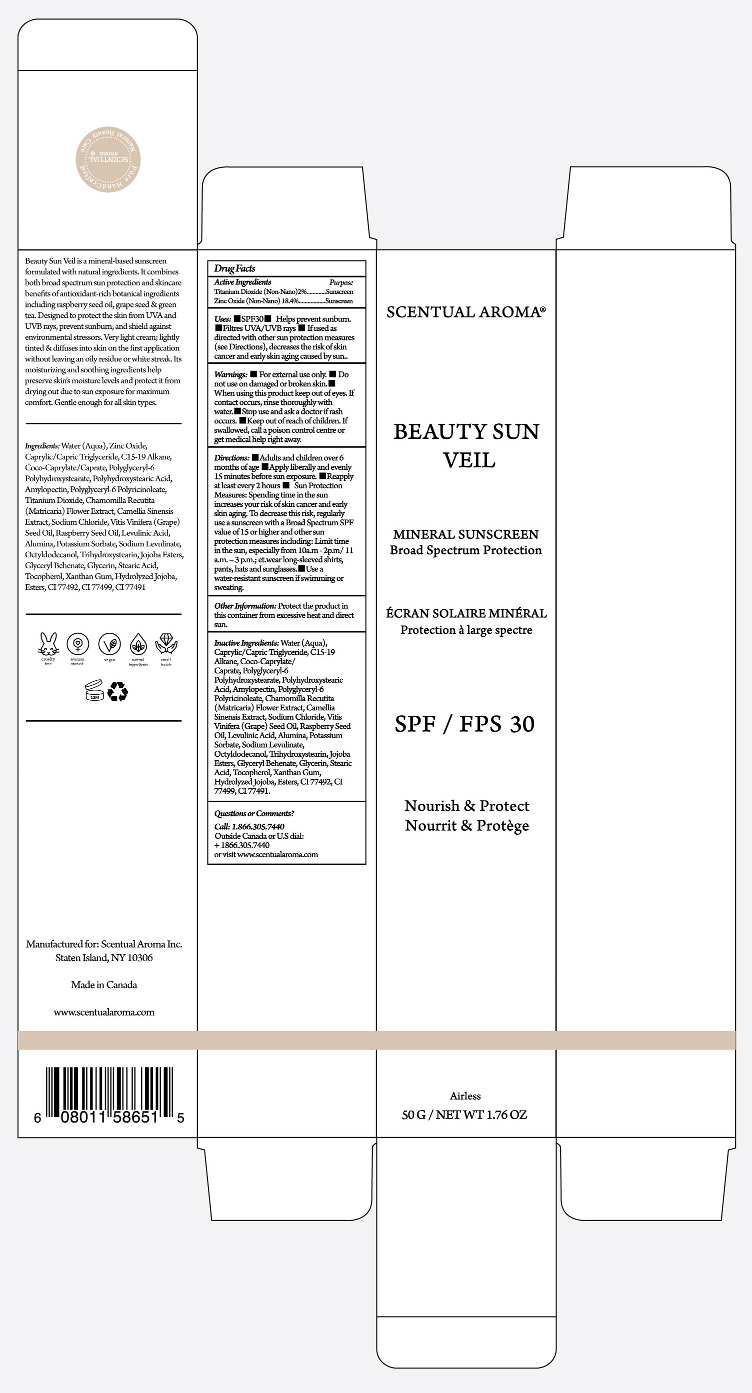 DRUG LABEL: SCENTUAL AROMA BEAUTY SUN VEIL
NDC: 71447-056 | Form: CREAM
Manufacturer: LABORATOIRES DRUIDE INC
Category: otc | Type: HUMAN OTC DRUG LABEL
Date: 20260114

ACTIVE INGREDIENTS: TITANIUM DIOXIDE 2 g/100 g; ZINC OXIDE 18.4 g/100 g
INACTIVE INGREDIENTS: SYNTHETIC BEESWAX; RASPBERRY SEED OIL; GLYCERYL BEHENATE/EICOSADIOATE; STEARIC ACID; TOCOPHEROL; COCO-CAPRYLATE; GLYCERIN; POLYHYDROXYSTEARIC ACID (2300 MW); XANTHAN GUM; POTASSIUM SORBATE; CAPRYLIC/CAPRIC/LINOLEIC TRIGLYCERIDE; MATRICARIA RECUTITA FLOWERING TOP; GRAPE SEED OIL; FERRIC OXIDE RED; JOJOBA OIL, RANDOMIZED; FERROSOFERRIC OXIDE; AMYLOPECTIN, UNSPECIFIED SOURCE; OCTYLDODECANOL; TRIHYDROXYSTEARIN; C15-19 ALKANE; ALUMINUM OXIDE; LEVULINIC ACID; POLYGLYCERYL-6 POLYRICINOLEATE; SODIUM CHLORIDE; CAMELLIA SINENSIS SEED OIL; WATER; SODIUM LEVULINATE; FERRIC OXIDE YELLOW; HYDROGENATED JOJOBA OIL, RANDOMIZED

SCENTUAL AROMA BEAUTY SUN VEIL MINERAL SUNSCREEN FPS30 50 MG

Active Ingredients

Titanium Dioxide 2.0%
Zinc Oxide 18.4%

Purpose

Sunscreen

Uses

▪ Helps prevent sunburn. ▪ If used as directed with other sun protection measures (see Directions), decreases the risk of skin cancer and early skin aging caused by the sun.

Warnings

For external use only

Do not use

on damaged or broken skin.

When using this product

keep out of eyes. Rinse with water to remove.

Stop use and ask a doctor if

rash occurs.

Keep out of reach of children

If swallowed, get medical help or contact Poison Control Center right away.

Directions

▪ Apply liberally and evenly 15 minutes before sun exposure ▪ Reapply ▪ After 80 minutes of swimming or
sweating ▪ Immediately after towel drying ▪ At least every 2 hours ▪ Sun Protection Measures▪ Spending
time in the sun increases your risk of skin cancer and early skin aging. To decrease this risk, regularly
use a sunscreen with a Broad Spectrum SPF value of 15 or higher and other sun protection measures
including: ▪ Limit time in the sun, especially from 10 a.m. - 2 p.m. ▪ Wear long-sleeved shirts, pants,
hats, and sunglasses ▪ Use a water-resistant sunscreen if swimming or sweating.

Other Information

Protect the product in this container from excessive heat and direct sun.

Inactive Ingredients

Water (Aqua), Caprylic/Capric Triglyceride, C15-19 Alkane, Coco-Caprylate/Caprate/Polyglyceryl-6 Polyhydroxystearate, Polyhydroxystearic Acid, Amylopectin, Polyglyceryl-6 Polyricinoleate, Chamomilla Recutita (Matricaria) Flower Extract, Camellia Sinensis Extract, Sodium Chloride, Vitis Vinifera (Grape) Seed Oil, Raspberry Seed Oil, Levulinic Acid, Alumina, Potassium Sorbate, Sodium Levulinate, Octyldodecanol, Trihydroxystearin, Jojoba Esters, Glyceryl Behenate, Glycerin, Stearic Acid, Tocopherol, Xanthan Gum, Hydrolyzed Jojoba, Esters, CI 77492, CI 77499, CI 77491 .

*Certified Organic.

Questions or Comments?

1-866-305-7440
or visit www.scentualaroma.com